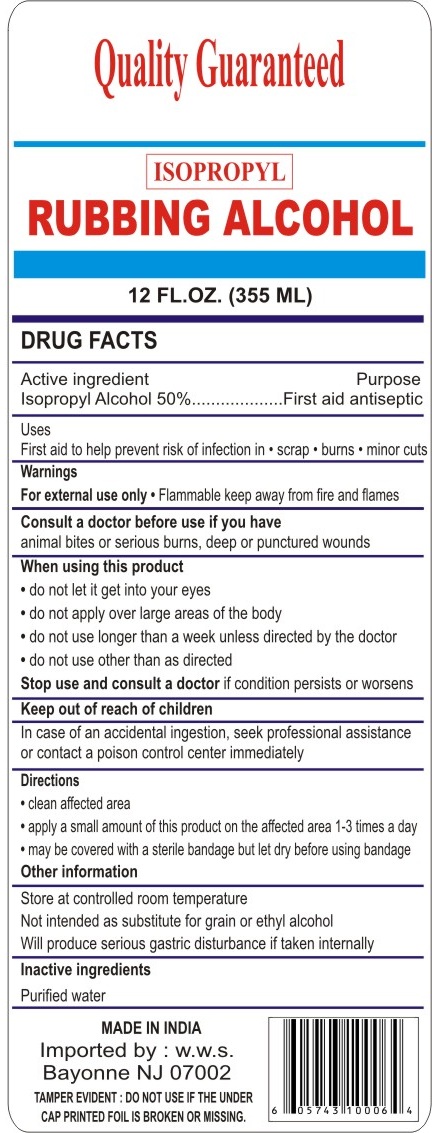 DRUG LABEL: ISOPROPYL RUBBING ALCOHOL
                        
NDC: 76384-005 | Form: LIQUID
Manufacturer: Worldwide Sales & Distribution Corp.
Category: otc | Type: HUMAN OTC DRUG LABEL
Date: 20110825

ACTIVE INGREDIENTS: ISOPROPYL ALCOHOL 50 mL/100 mL
INACTIVE INGREDIENTS: WATER 50 mL/100 mL

Quality Guaranteed RUBBING ALCOHOL

Drug Facts

Active Ingredients

Isopropyl Alcohol 50%

Purpose

First aid antiseptic

Uses

First aid to help prevent risk of infection in

- scrap
- burns
- minor cuts

Warnings

For external use only

- Flammable keep away from fire and flames

ASK DOCTOR/PHARMACIST

Consult a doctor before use if you have animal bites or serious burns, deep or punctured wounds

When using this product

- do not let it get into your eyes
- do not apply over large areas of the body
- do not use longer than a week unless directed by the doctor
- do not use other than as directed

Stop use and ask a doctor if condition persists or worsens

Keep out of reach of children. In case of an accidental ingestion, seek professional assistance or contact a poison control center immediately.

Directions

- clean affected area
- apply a small amount of this product on the affected area 1-3 times a day
- may be covered with a sterile bandage but let dry before using bandage

Other information

- Store at controlled room temperature
- Not intended as substitute for grain or ethyl alcohol
- Will produce serious gastric disturbance if taken internally

Inactive ingredient

Purified water